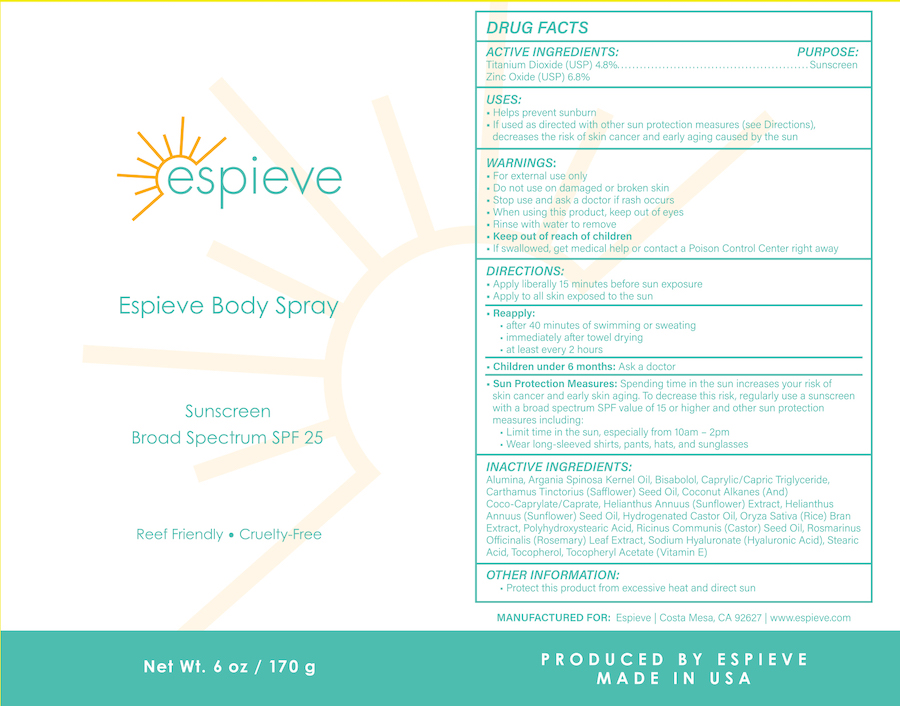 DRUG LABEL: Tru Skin Rituals SPF 25
NDC: 68062-8801 | Form: SPRAY
Manufacturer: Spa de Soleil
Category: otc | Type: HUMAN OTC DRUG LABEL
Date: 20230318

ACTIVE INGREDIENTS: TITANIUM DIOXIDE 8.16 mg/170 mL; ZINC OXIDE 11.56 mg/170 mL
INACTIVE INGREDIENTS: SAFFLOWER OIL; CAPRYLIC/CAPRIC/LAURIC TRIGLYCERIDE; ALUMINUM OXIDE; COCONUT ALKANES; ARGANIA SPINOSA SEED; .BETA.-BISABOLOL

Tru Skin Rituals SPF 25

Active Ingredients

Titanium Dioxide 4.8%

Zinc Oxide 6.8%

Purpose

Sunscreen

Warnings

- For external use only
- Do not use on damaged or broken skin
- Stop use and ask a doctor if rash occurs
- When using this product, keep out of eyes
- Rinse with water to remove
- Keep out of reach of children
- If swallowed, get medical help or contact a Poison Control Center right away

Directions

- Apply liberally 15 minutes before sun exposure
- Apply to all skin exposed to the sun

Inactive Ingredients

Alumina, Argania Spinosa Kernel Oil, Bisabolol, Caprylic/Capric Triglyceride, Carthamus Tinctorius (Safflower) Seed Oil, Coconut Alkanes (And) Coco-Caprylate/Caprate, Helianthus Annuus (Sunflower) Extract, Helianthus Annuus (Sunflower) Seed Oil, Hydrogenated Castor Oil, Oryza Sativa (Rice) Bran Extract, Polyhydroxystearic Acid, Ricinus Communis (Castor) Seed Oil, Rosmarinus Officinalis (Rosemary) Leaf Extract, Sodium Hyaluronate (Hyaluronic Acid), Stearic Acid, Tocopherol, Tocopheryl Acetate (Vitamin E)

Keep out of reach of children

DIRECTIONS:

• Apply liberally 15 minutes before sun exposure

• Apply to all skin exposed to the sun

Reapply:

• after 40 minutes of swimming or sweating

• immediately after towel drying

• at least every 2 hours